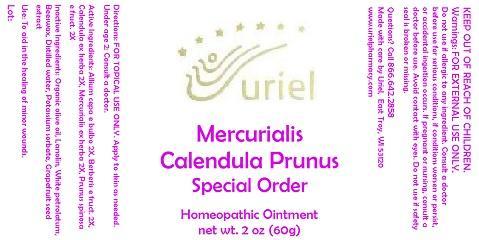 DRUG LABEL: Mercurialis Calendula Prunus Special Order
NDC: 48951-7127 | Form: OINTMENT
Manufacturer: Uriel Pharmacy Inc.
Category: homeopathic | Type: HUMAN OTC DRUG LABEL
Date: 20140929

ACTIVE INGREDIENTS: ONION 2 [hp_X]/1 g; BERBERIS VULGARIS ROOT BARK 2 [hp_X]/1 g; CALENDULA OFFICINALIS FLOWERING TOP 2 [hp_X]/1 g; MERCURIALIS PERENNIS 2 [hp_X]/1 g; SLOE 2 [hp_X]/1 g
INACTIVE INGREDIENTS: OLIVE OIL; LANOLIN; PETROLATUM; YELLOW WAX; WATER; POTASSIUM SORBATE; CITRUS PARADISI SEED

Mercurialis Calendula Prunus Special Order

INDICATIONS AND USAGE

Directions: FOR TOPICAL USE ONLY.

DOSAGE AND ADMINISTRATION

Apply to skin as needed. Under age 2: Consult a doctor.

ACTIVE INGREDIENT

Active Ingredients: 100 gm contains: 20 gm Allium cepa e bulbo 1X, 30 gm Calendula ex herba 1X, 50 gm Mercurialis ex herba 1X; Berberis e fruct. 3X, Prunus spinosa e fruct. 3X, Peruvian balsam 5X/15X, Aurum metallicum 8X, Stibium metallicum 10X

INACTIVE INGREDIENT

Inactive Ingredients: Organic olive oil, Lanolin, White petrolatum, Beeswax, Distilled water, Peruvian balsam, Potassium sorbate, Grapefruit seed extract

PURPOSE

Use: To aid in the healing of minor wounds.

KEEP OUT OF REACH OF CHILDREN.

WARNINGS

Warnings: FOR EXTERNAL USE ONLY. Do not use if allergic to any ingredient. Consult a doctor before use for serious conditions, if conditions worsen or persist, or accidental ingestion occurs. If pregnant or nursing, consult a doctor before use. Avoid contact with eyes. Do not use if safety seal is broken or missing.

QUESTIONS

Questions? Call 866.642.2858 Made with care by Uriel, East Troy, WI 53120 www.urielpharmacy.com